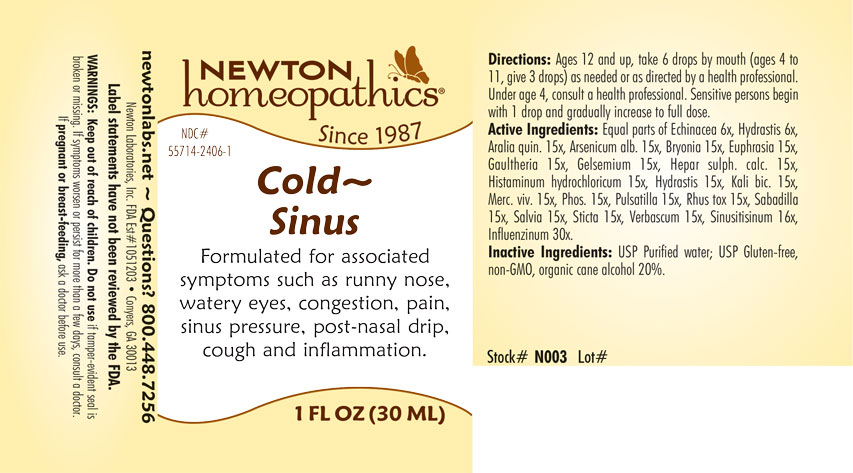 DRUG LABEL: Cold - Sinus
NDC: 55714-2406 | Form: LIQUID
Manufacturer: Newton Laboratories, Inc.
Category: homeopathic | Type: HUMAN OTC DRUG LABEL
Date: 20220317

ACTIVE INGREDIENTS: SINUSITISINUM 16 [hp_X]/1 mL; INFLUENZA A VIRUS 30 [hp_X]/1 mL; AMERICAN GINSENG 15 [hp_X]/1 mL; ARSENIC TRIOXIDE 15 [hp_C]/1 mL; BRYONIA ALBA ROOT 15 [hp_X]/1 mL; EUPHRASIA STRICTA 15 [hp_X]/1 mL; GAULTHERIA PROCUMBENS TOP 15 [hp_X]/1 mL; GELSEMIUM SEMPERVIRENS ROOT 15 [hp_X]/1 mL; CALCIUM SULFIDE 15 [hp_X]/1 mL; HISTAMINE DIHYDROCHLORIDE 15 [hp_X]/1 mL; GOLDENSEAL 15 [hp_X]/1 mL; POTASSIUM DICHROMATE 15 [hp_X]/1 mL; MERCURY 15 [hp_X]/1 mL; PHOSPHORUS 15 [hp_X]/1 mL; PULSATILLA VULGARIS 15 [hp_X]/1 mL; TOXICODENDRON PUBESCENS LEAF 15 [hp_X]/1 mL; SCHOENOCAULON OFFICINALE SEED 15 [hp_X]/1 mL; SAGE 15 [hp_X]/1 mL; LOBARIA PULMONARIA 15 [hp_X]/1 mL; VERBASCUM THAPSUS 15 [hp_X]/1 mL; ECHINACEA, UNSPECIFIED 6 [hp_X]/1 mL; INFLUENZA B VIRUS 30 [hp_X]/1 mL
INACTIVE INGREDIENTS: ALCOHOL; WATER

ColdSi 2406L

OTC - PURPOSE SECTION

Formulated for associated symptoms such as runny nose, watery eyes, congestion, pain, sinus pressure, post-nasal drip, cough and inflammation.

OTC - KEEP OUT OF REACH OF CHILDREN SECTION

Keep out of reach of children.

OTC - PREGNANCY OR BREAST FEEDING SECTION

If pregnant or breast-feeding, ask a doctor before use.

WARNINGS SECTION

WARNGINGS: Keep out of reach of children. Do not use if tamper-evident seal is broken or missing. If symptoms worsen or persist for more than a few days, consult a doctror. If pregnant or breast-feeding, ask a doctor before use.

QUESTIONS SECTION

newtonlabs.net - Questions? 800 448-7256

Newton Laboratories, Inc. FDA Est # 1051203 - Conyers, GA 30013

INACTIVE INGREDIENT SECTION

USP Purified water, USP Gluten-free, non-GMO, organic cane alcohol 20%.

OTC - ACTIVE INGREDIENT SECTION

Equal parts of Echinacea 6x, Hydrastis 6x, Aralia quin. 15x, Arsenicum alb. 15x, Bryonia 15x, Euphrasia 15x, Gaultheria 15x, Gelsemium 15x, Hepar sulph. calc. 15x, Histaminum hydrochloricum 15x, Hydrastis 15x, Kali bic. 15x, Merc. viv. 15x, Phos. 15x, Pulsatilla 15x, Rhus tox. 15x, Sabadilla 15x, Salvia 15x, Sticta 15x, Verbascum 15x, Sinusitisinum 16x, Influenzinum 30x.

INDICATIONS & USAGE SECTION

Formulated for associated symptoms such as runny nose, watery eyes, congestion, pain, sinus pressure, post-nasal drip, cough and inflammation.

DOSAGE & ADMINISTRATION SECTION

Ages 12 and up, take 6 drops by mouth (ages 4 to 11, give 3 drops) as needed or as directed by a health professional. Under age 4, consult a health professional. Sensitive persons begin with 1 drop and gradually increase to full dose.